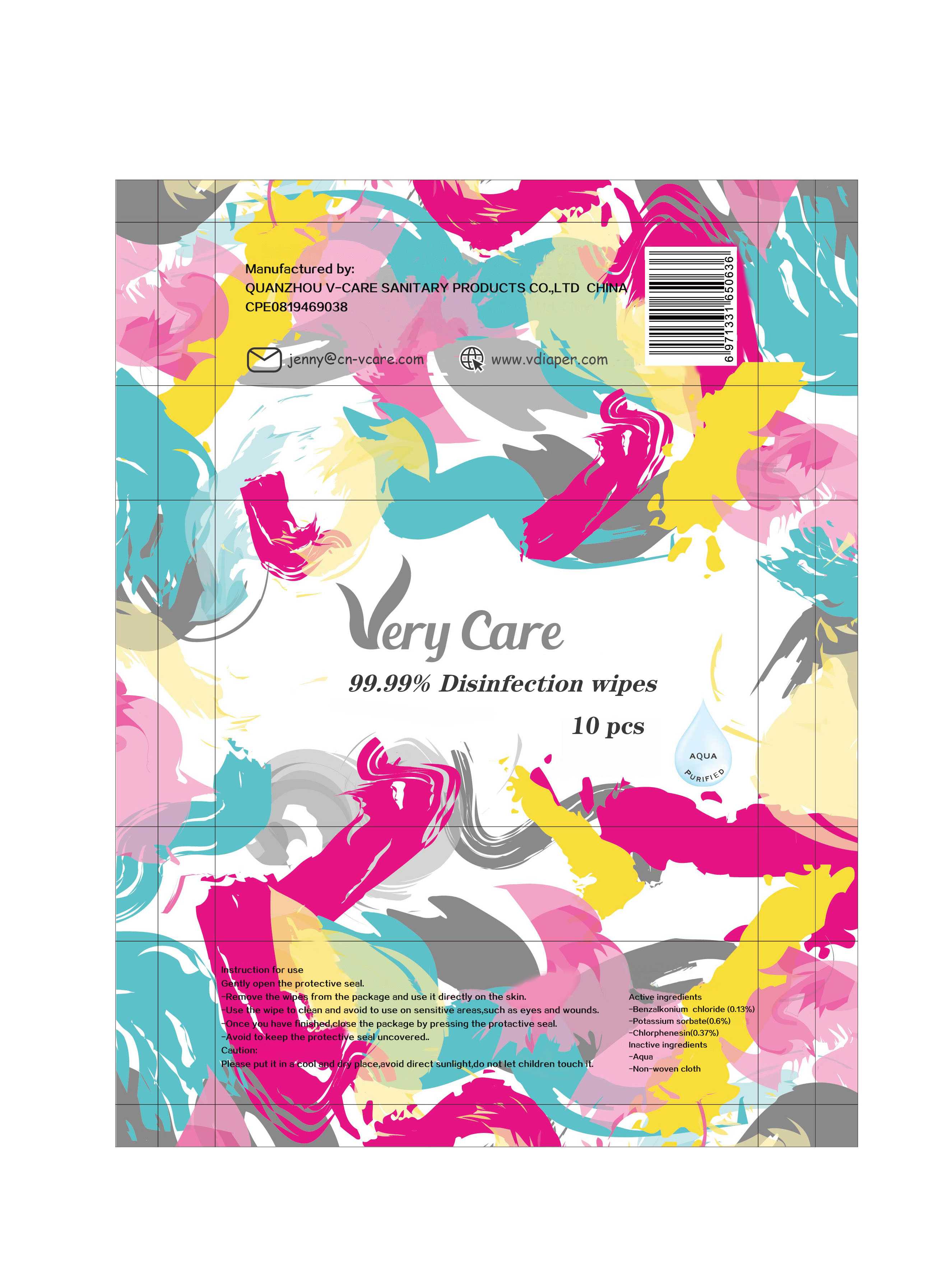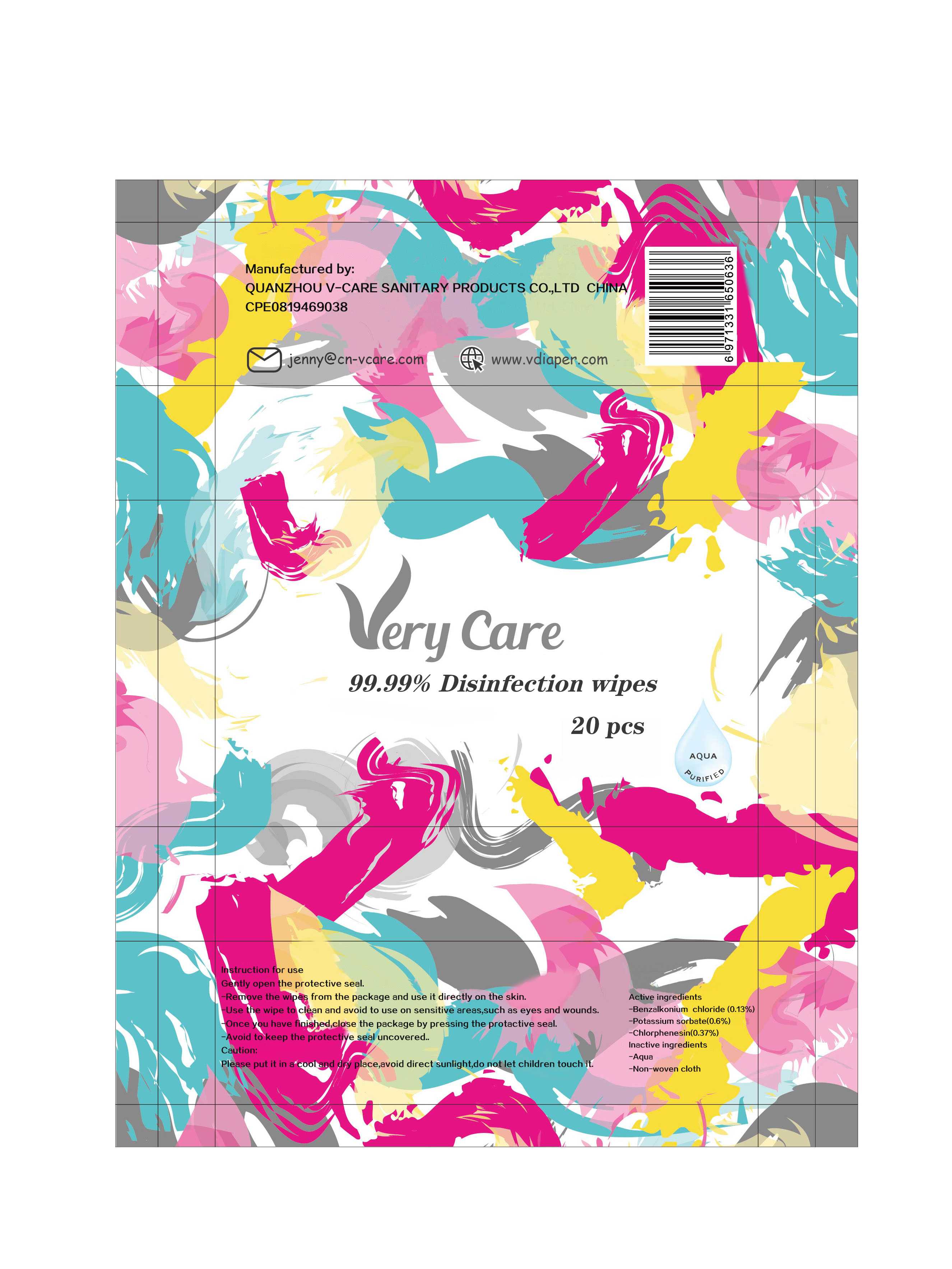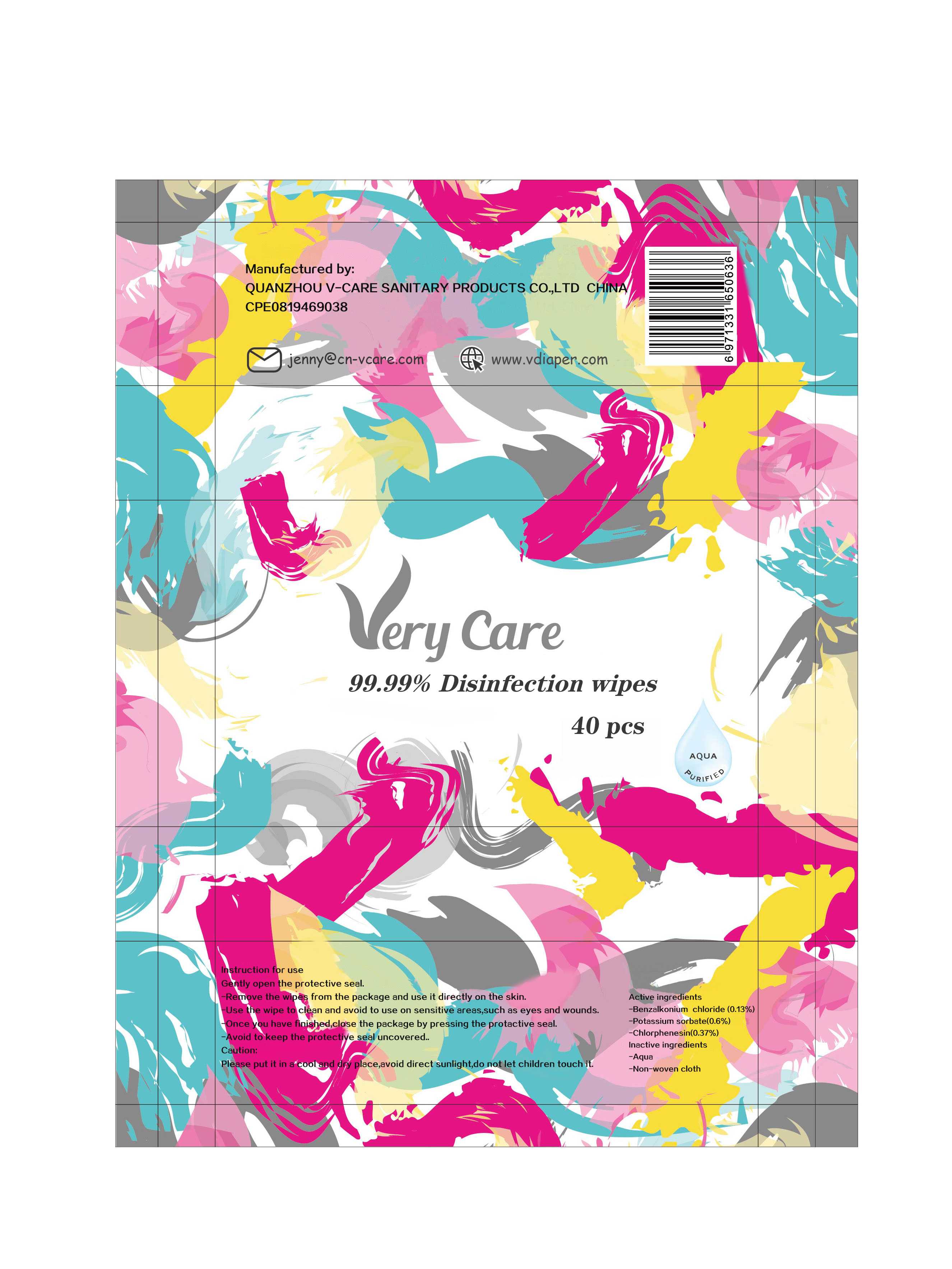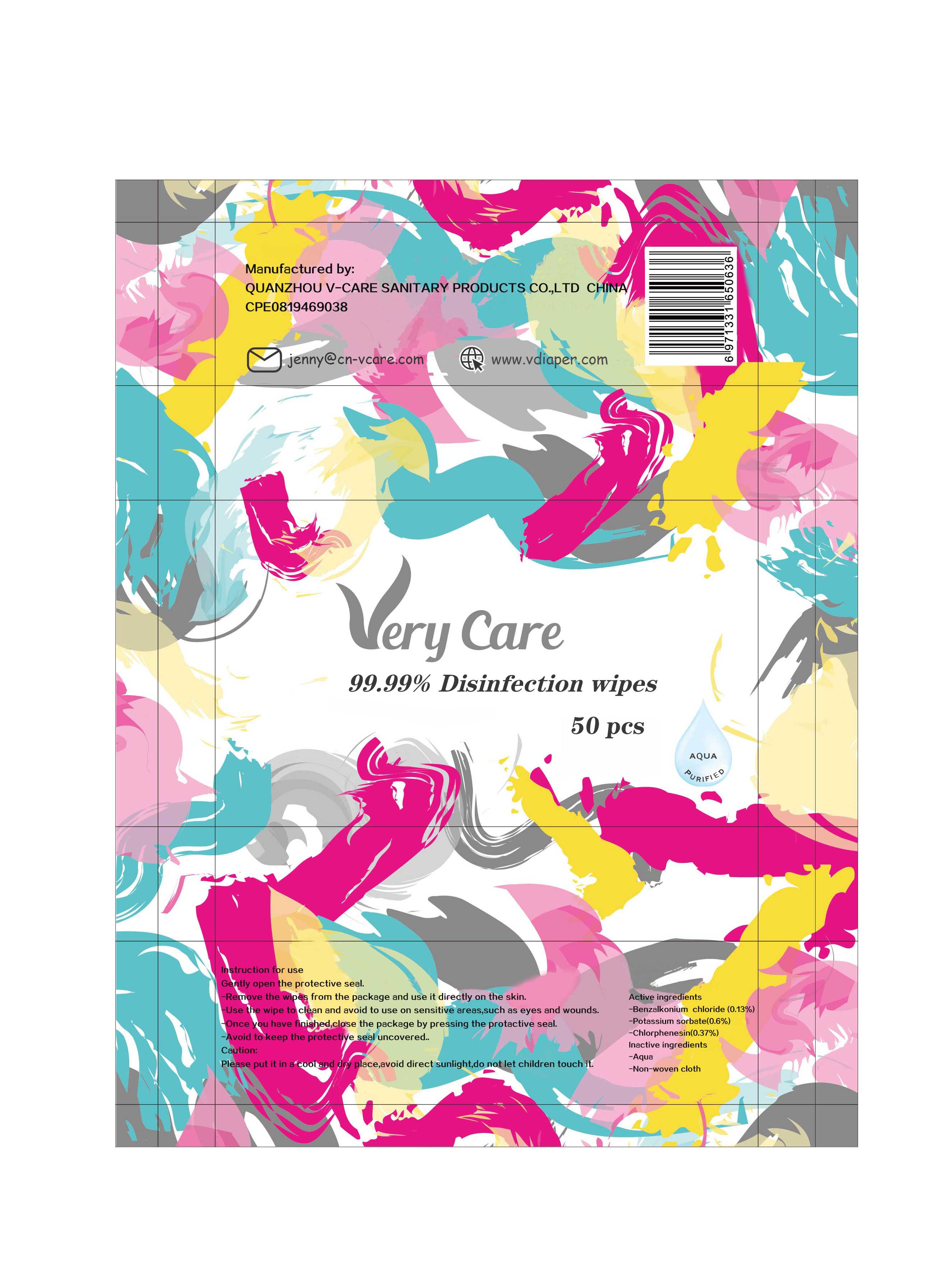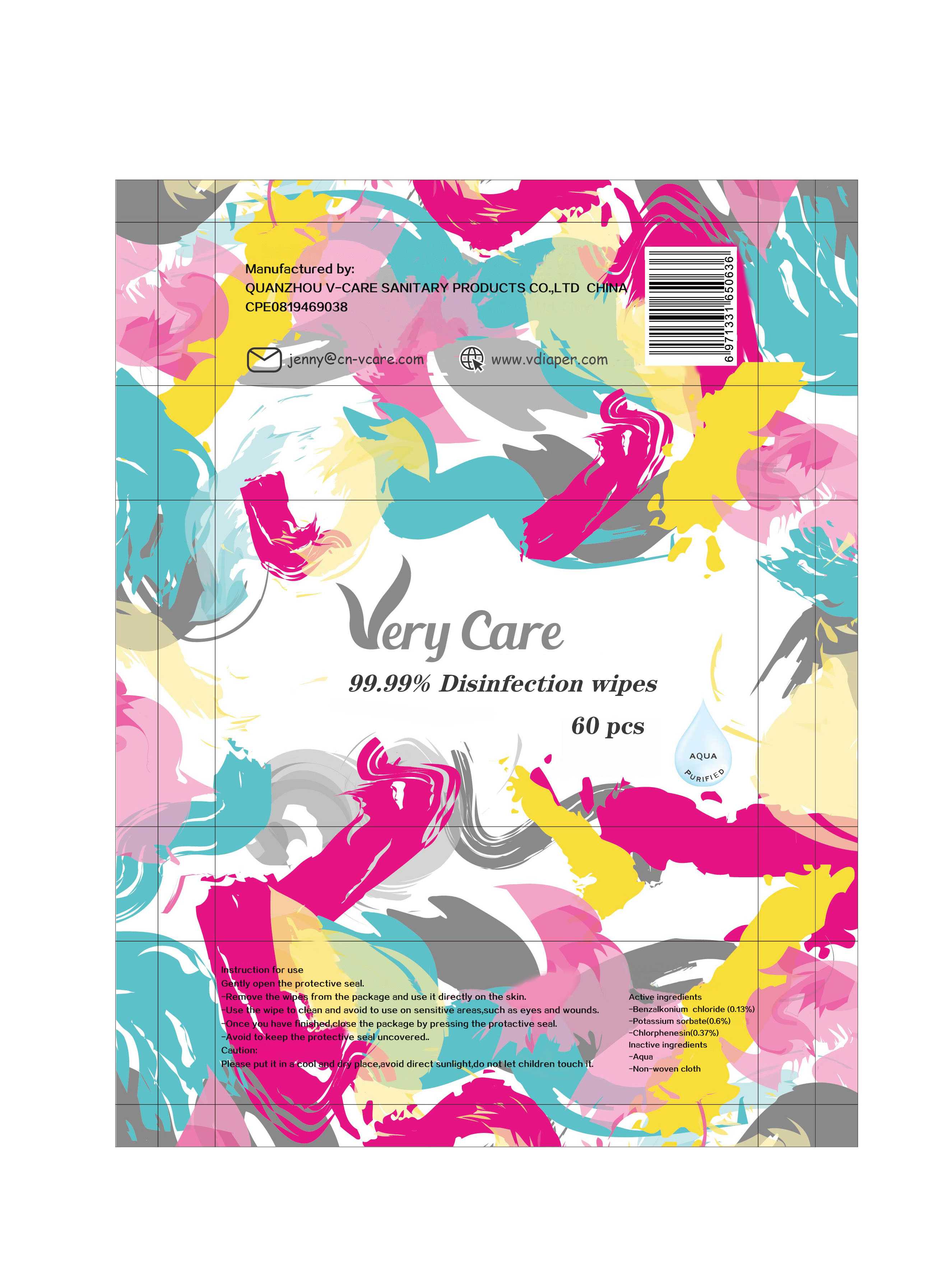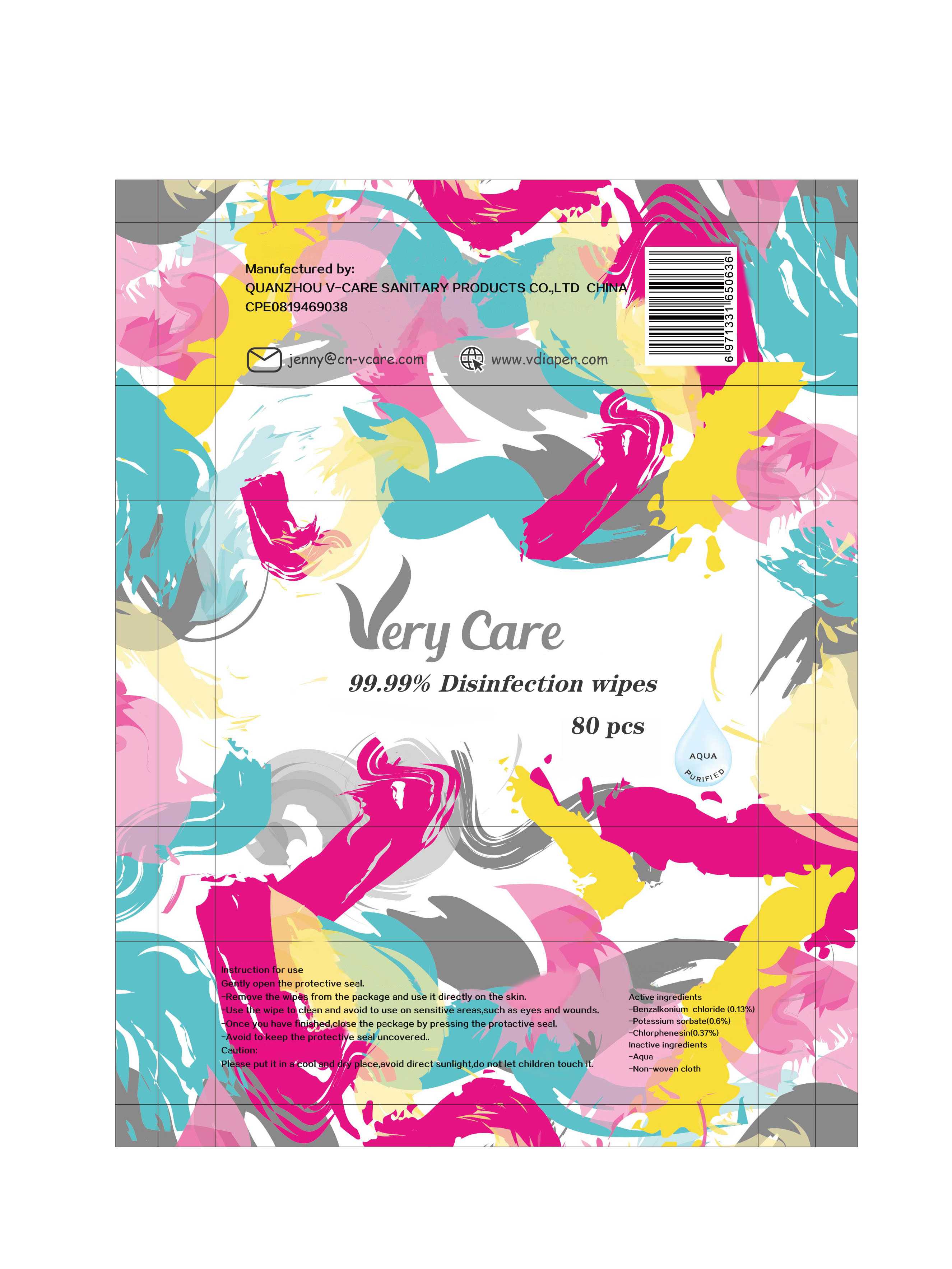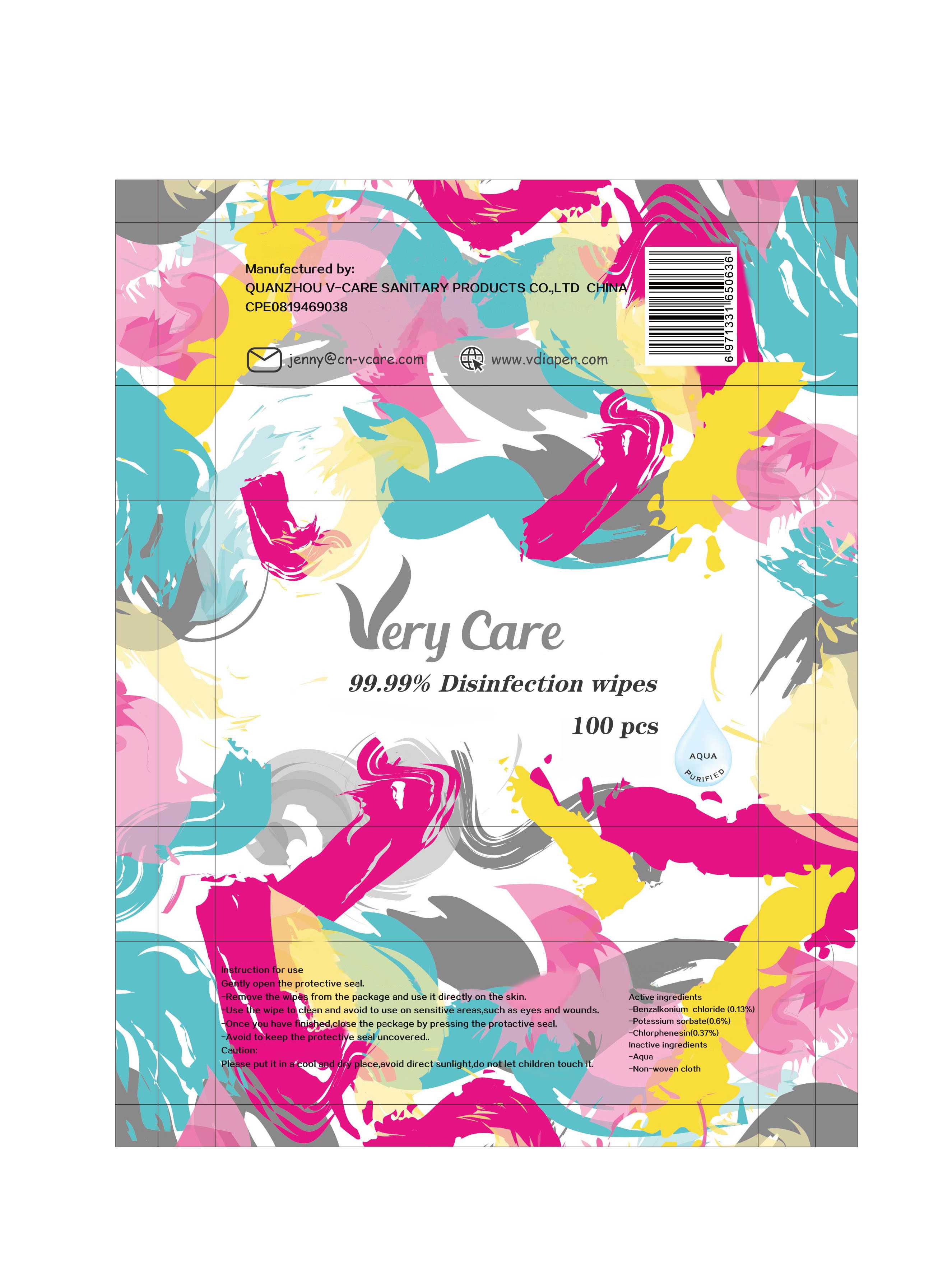 DRUG LABEL: 99.99% Disinfection wipes
NDC: 80515-002 | Form: CLOTH
Manufacturer: QUANZHOU V-CARE SANITARY PRODUCTS CO.,LTD
Category: otc | Type: HUMAN OTC DRUG LABEL
Date: 20200904

ACTIVE INGREDIENTS: BENZALKONIUM CHLORIDE 0.13 g/100 1; POTASSIUM SORBATE 0.6 g/100 1; CHLORPHENESIN 0.37 g/100 1
INACTIVE INGREDIENTS: WATER

80515-002
99.99% Disinfection wipes

Active Ingredient(s)

Benzalkonium chloride (0.13%)
Potassium sorbate(0.6%)
Chlorphenesin(0.37%)

Purpose

/

Use

Instruction for use

Warnings

When using this product
Caution:Please put it in a cootapd dry place, avoid direct sunlight, do not let children touch it

Do not use

/

WHEN USING

Caution:Please put it in a cootapd dry place, avoid direct sunlight, do not let children touch it

STOP USE

/

KEEP OUT OF REACH OF CHILDREN

/

Directions

Gently open the protective seal
Remove the wipes from the package and use it directly on the skin
Use the wipe to clean and avoid to use on sensitive areas, such as eyes and wounds
Once you have finished, close the package by pressing the protactive seal
Avoid to keep the protective seal uncovered

Other information

/

Inactive ingredients

Aqua(75%)